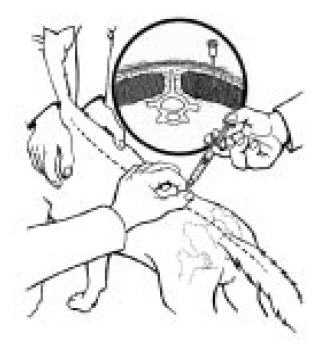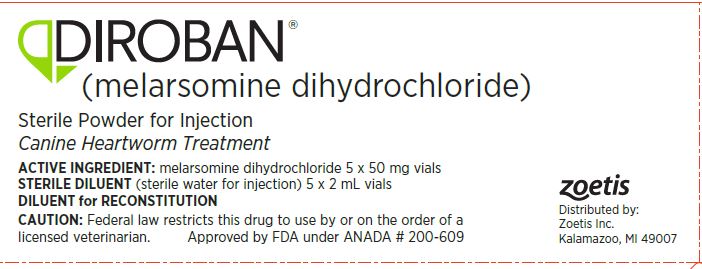 DRUG LABEL: DIROBAN
NDC: 54771-1920 | Form: KIT | Route: INTRAMUSCULAR
Manufacturer: Zoetis Inc.
Category: animal | Type: PRESCRIPTION ANIMAL DRUG LABEL
Date: 20200505

ACTIVE INGREDIENTS: MELARSOMINE DIHYDROCHLORIDE 50 mg/2 mL
INACTIVE INGREDIENTS: GLYCINE; WATER

DIROBAN®
(melarsomine dihydrochloride)

Sterile Powder for Injection

Canine Heartworm Treatment

CAUTION

Federal law restricts this drug to use by or on the order of a licensed veterinarian.

WARNING

DIROBAN® should be administered by deep intramuscular injection in the epaxial (lumbar) muscles (L3 - L5) ONLY.
DO NOT USE IN ANY OTHER MUSCLE GROUP.
DO NOT USE INTRAVENOUSLY.
Care should be taken to avoid superficial injection or leakage (see SAFETY).

ACTIVE INGREDIENT

DIROBAN Sterile Powder for Injection contains 50.0 mg melarsomine dihydrochloride and 33.75 mg glycine USP.

1 vial: when reconstituted with 2 mL of sterile water for injection (provided) contains 25 mg/mL of active ingredient.

PHARMACOLOGY

Melarsomine dihydrochloride is an organic arsenical chemotherapeutic agent. Melarsomine has a molecular weight of 501.34 and is chemically designated as 4 - [(4, 6-diamino-1, 3, 5- triazon-2-yl) amino] phenyldithioarsenite of di (2-aminoethyl), dihydrochloride. It is freely soluble in water. When injected intramuscularly, it is rapidly absorbed. The exact mode of action on D. immitis is unknown.

INDICATIONS

DIROBAN Sterile Powder for Injection is indicated for the treatment of stabilized Class 1a, 2b, and 3c heartworm disease caused by immature (4 month-old, stage L5) to mature adult infections of Dirofilaria immitis in dogs.

Heartworm Disease Classification: The following parameters were used to classify the dogs in the clinical field trials for DIROBAN. Other parameters may be considered. As a general rule, conservative treatment should be employed since heartworm
disease is serious and potentially fatal. If there is evidence of a high worm burden, patients should be categorized as Class 3.

a Class 1: Patients in this category are characterized as having asymptomatic to mild heartworm disease. No radiographic signs or signs of anemia are evident. Patients with mild disease may have subjective signs such as a general loss of condition, fatigue on exercise, or occasional cough; however, no objective radiographic or other abnormal laboratory parameters will be present.

b Class 2: Patients in this category are characterized as having moderate heartworm disease. Radiographic signs or signs of anemia [Packed Cell Volume (PCV) less than 30% but greater than 20%, or other hematologic parameters below normal] are evident. Mild proteinuria (2+) may be present. Radiographic signs may include right ventricular enlargement, slight pulmonary artery enlargement,
or circumscribed perivascular densities plus mixed alveolar/interstitial lesions. Patients may be free of subjective clinical signs or may have a general loss of condition, fatigue on exercise, or occasional If necessary, patients should be stabilized prior to treatment.

c Class 3: Patients in this category are characterized as having severe heartworm disease. These patients have a guarded prognosis. Subjective signs of disease may include cardiac cachexia (wasting), constant fatigue, persistent cough, dyspnea, or other signs associated with right heart failure such as ascites and/or jugular pulse. Radiographic signs may include right ventricular enlargement or right ventricular plus right atrial enlargement, severe pulmonary artery enlargement, circum- scribed to chronic mixed patterns and diffuse patterns of pulmonary densities or radiographic signs of throm boembolism. Signs of significant anemia (PCV <20% or other hematologic abnormalities) may be present. Proteinuria (> 2+) may be present. Patients may have only moderate clinical signs and significant laboratory or radiographic alterations or they may have significant clinical signs with only moderate laboratory and radio- graphic signs and be categorized as Class 3. Patients in Class 3 should be stabilized prior to treatment and then administered the alternate dosing regime (see PRECAUTIONS and DOSAGE AND ADMINISTRATION).

CONTRAINDICATIONS

DIROBAN is contraindicated in dogs with very severe (Class 4) heartworm disease. Patients in this category have Caval Syndrome (D immitis present in the venae cavae and right atrium).

WARNINGS

(See boxed Warning.) For use in dogs only. Safety for use in breeding animals and lactating or pregnant bitches has not been determined.

HUMAN WARNINGS

Keep this and all medications out of the reach of children. Avoid human exposure. Wash hands thoroughly after use or wear gloves. Potentially irritating to eyes. Rinse eyes with copious amounts of water if exposed. Consult a physician in cases of accidental exposure by any route (dermal, oral, or by injection).
The Safety Data Sheet (SDS) contains more detailed occupational safety information. To report suspected adverse drug events, for technical assistance or to obtain a copy of the SDS, contact Zoetis Inc. at 1-888-963-8471. For additional information about adverse drug experience reporting for animal drugs, contact FDA at 1-888-FDA-VETS or online at www.fda.gov/reportanimalae.

PRECAUTIONS

General

All dogs with heartworm disease are at risk for post-treatment pulmonary thromboembolism (death of worms which may result in fever, weakness, and coughing), though dogs with severe pulmonary arterial disease have an increased risk and may exhibit more severe signs (dyspnea, hemoptysis, right heart failure and possibly death). Dogs should be restricted from light to heavy exercise post-treatment depending on the severity of their heartworm disease.
Studies in healthy (heartworm negative) dogs indicate that adverse reactions may occur after the second injection in the series even if no problems were encountered with the first injection. All patients should be closely during treatment and for up to 24 hours after the last injection.

Special Considerations for Class 3 dogs

Following stabilization, severely ill (Class 3) dogs should be treated according to the alternate dosing regime in an attempt to decrease post-treatment mortality associated with thromboembolism (see DOSAGE AND ADMINISTRATION). Post-treatment mortality due to
thromboembolism and/or progression of the underlying disease may occur in 10 to 20% of the Class 3 patients treated with DIROBAN (see Mortality). Hospitalization post-treatment and strict exercise restriction are recom- mended. Other supportive therapies should be consid- ered on a case-by-case basis.

If the alternate dosing regime is used, expect increased injection site reactions on the side receiving the second injection since the skeletal muscles at the first injection site may not have fully recovered (healed). If persistent swelling is present at 1 month, the second injections may be delayed for several weeks up to 1 month.

Special Considerations for Older Dogs

In clinical field trials, dogs 8 years or older experienced more posttreatment depression/lethargy, anorexia/inappetence, and vomiting than younger dogs.

SAFETY

Melarsomine dihydrochloride has a low margin of safety. A single dose of 7.5 mg/kg (3X the recommended dose) can result in pulmonary inflammation, edema, and death. Daily administration of 2X and 3X the recommended dose for 6 days caused no renal injury; however, daily administration of these doses for 14 days caused renal damage in healthy dogs. Adverse reactions, primarily at the injection sites, were seen at the recommended dose in clinical trials (see ADVERSE REACTIONS).

Studies in Healthy (Heartworm Negative) Dogs

The safety of melarsomine dihydrochloride was studied in 24 healthy beagle dogs. Drug was administered
at 0, 2.5, 5.0, and 7.5 mg/kg for 6 consecutive days (0, 1, 2, and 3 times the recommended dosage). Clinical observations included tremors, lethargy, unsteadiness/ ataxia, restlessness, panting, shallow and labored respiration, and/or rales. These
signs were seen in all groups treated with melarsomine dihydrochloride with frequency and intensity
increasing with increasing dosage. Death or euthanasia in a moribund state occurred in 3/6 dogs in
the 7.5 mg/kg (3X) group. The signs exhibited by these dogs, in addition to the signs described
above, included collapse, severe salivation, vomiting, respiratory distress, cyanosis, stupor, and
death within 4 hours of the first dose in two dogs and within 20 hours of the second dose in one dog.

Body weights, water consumption, hematology and urine parameters were comparable to controls.
Decreased food consumption occurred sporadically in the two high dose groups. Elevations, up to
25-fold, in creatinine kinase (CK) and elevations, up to 7-fold, in aspartate aminotransferase
(AST) were observed and related grossly and histologically to muscle damage at the injection sites. Up to 2-fold
elevations in alanine aminotransferase (ALT) were also noted. Gross and microscopic pathology
revealed no organ-related toxicity other than edema and acute inflammation in the lungs and pleural
effusion in the 3 dogs that died at the 7.5 mg/kg dose. Injection site irritation was observed in the skeletal muscles at all dose levels.
At 5.0 mg/kg an injection site abscess was observed in one dog.

A separate study was conducted to examine the inten- sity and duration of injection site reactions.
The dogs were dosed at 2.5 and 5.0 mg/kg (1X and 2X the recommended dose) twice 24 hours apart.
This treat- ment series was repeated 4 months later. One group received the second treatment series
after 1 month to mimic the alternate dosing regime. Swelling, which occurred within 7 days of
injection and persisted from 1 to 72 days (average 30 days), was the most common clinical
observation. A small, firm nodule in the lumbar region of one dog in the 1X group appeared during
the first month of the study and persisted for 41 days. Pain at or following injection was not observed in this study. Elevations of the same magnitude as in the previous study and again related to muscle damage were observed in CK and AST within 8 hours of
injection. The values approached pretest levels by 72 hours and were within the normal range established by control animals by
1 month post-injection.

Gross and microscopic evidence of injection site irritation (cellular infiltrate, fibrosis,
necrosis, and hemorrhage) was still evident in the muscles 1 month post-injection in dogs at both
dose levels. By 3 months post-injection, resolution (healing) was evident micro- scopically in the
skeletal muscles at the 2.5 mg/kg dose level. One dog treated at the 2X dose had extension of
treatment-related injection site inflammation into deeper tissues (i.e., abdominal cavity) as evidenced by an adhesion between the spleen and mesentery.

ADVERSE REACTIONS (Side Effects)

Injection Sites: At the recommended dosage in clinical field trials, significant irritation was observed at the intramuscular injection sites, accompanied by pain, swelling, tenderness, and reluctance to move. Approximately 30% of treated dogs experienced some kind of reaction at the injection site(s). Though injection site reactions were generally mild to moderate in severity and recovery occurred in 1 week to 1 month, severe reactions did occur (< 1.0%), so care should be taken to avoid superficial or subcutaneous injection and leakage. Firm nodules can persist indefinitely.

Other Reactions

Coughing/gagging, depression/lethargy, anorexia/inappetence, fever, lung congestion, and vomiting were the most common reactions
observed in dogs treated with melarsomine dihydrochloride. Hypersalivation and panting occurred
rarely in clinical trials (1.9% and 1.6%, respectively); however, these signs may occur within
30 minutes of injection and may be severe. One dog vomited after each injection of melarsomine
dihydrochloride, despite pretreatment with anti-emetics. All adverse reactions resolved with time
or treatment with the exception of a limited number of injection site reac- tions (persistent
nodules, (see Table: Average Onset Time and Duration (with Ranges) of the Most Common Reactions in Clinical Trials) and a low number of posttreatment deaths (see Mortality).

Prevalence of Clinical Observations/Adverse Reactions Reported in Clinical Field Trials: The following table enumerates adverse events that occurred in 1.5% or more of dogs with Class 1, 2, and 3 heartworm disease treated with melarsomine
dihydrochloride in clinical field trials. Comparison is made with the same adverse events reported
in dogs treated with placebo. Some of the following clinical observations/adverse reactions seen in
dogs treated with melarsomine dihydrochloride may be directly attributable to the drug or they may be secondary to worm death and/or the underlying heartwormdisease process.

.

Prevalence of Clinical Observation/Adverse Reactions Reported in Clinical Field Trials
Clinical Observation/Adverse Reaction | Melarsomine dihydrochloride% of dogs n=311 | PLACEBO % of dogs n=63
Injection Site Reactions | 32.8 | 3.2
Coughing/Gagging | 22.2 | 14.3
Depression/Lethargy | 15.4 | 4.8
Anorexia/Inappetence | 13.2 | 3.2
Pyrexia (fever) | 7.4 | 0.0
Lung Congestion/Sounds | 5.5 | 1.6
Emesis | 5.1 | 1.6
Diarrhea | 2.6 | 0.0
Dyspnea | 2.6 | 1.6
Hypersalivation | 1.9 | 0.0
Panting | 1.6 | 0.0
Hemoptysis | 1.6 | 0.0

Clinical observations/adverse reactions occurring in
less than 1.5% of the dogs treated with melarsomine dihydrochloride include: abdominal hemorrhage,
abdominal pain, bloody stool/diarrhea, colitis, gingivitis, pancreatitis, anemia, DIC,
hemoglobinemia, icterus (mucous membranes), discolored urine, hematuria, inappropriate urination,
low specific gravity, polyuria, pyuria, bronchitis, miscellaneous respiratory problem, pneumonia,
tachypnea, tracheobronchitis, wheezing, alopecia, hair color and coat character change, miscella-
neous skin problem, ataxia, disorientation, fatigue/tires easily, miscellaneous eye problem, weight
loss, convul- sion/seizure, leukocytosis, polydipsia, and restlessness.

Onset and Duration of Clinical Observations/Adverse Reactions

The following table is provided to show the average onset time post-treatment for the most common reactions and the average duration of each event, as calculated from the 311 dogs treated with melarsomine dihydrochloride in the clinical field trials.

Average Onset Time and Duration (with Ranges) of the Most Common Reactions in Clinical Trials
Clinical Observation/Adverse Reaction | Avg. Onset Time in Days (range)* | Avg. Duration in Days (range)*
Injection Site
Swelling/Edema/Seroma | 6 (0*-77) | 18 (<1-210)
Pain/Discomfort/Irritation/Inflammation/Heat | 1 (0-6) | 3 (<1-30)
Generalized/Local Myalgia with Tenderness and Stiffness | 3 (1-8) | 9 (<1-30)
Persistent (lumps, knots, nodules, masses) | 22 (0-99) | 47 (1-152)
Abscess (sterile and septic) | 24 (10-42) | 21 (5-36)
Coughing/Gagging | 10 (0-103) | 13 (<1-134)
Depression/Lethargy | 5 (0-46) | 6 (<1-48)
Anorexia/Inappetence | 5 (0-63) | 5 (<1-30)

* A zero indicates that the reaction first occurred on the day of treatment.

Mortality

Death is a possible sequelae of heartworm disease in dogs with or without treatment, especially in the Class 3 dogs. The following table shows the percentage of dogs that died in clinical trials with melarsomine dihydrochloride and the causes of death, if known.

Mortality in Dogs with Class 1, 2, and 3 Heartworm Disease Treated with melarsomine dihydrochloride in Clinical Field Trials
 |  | CLASS 1, 2 % OF DOGS n=267 | CLASS 3 % OF DOGS n=44
Total Deaths |  | 5.2 | 18.2
Cause: | Trauma | 2.3 | 2.3
 | Thromboembolism | 0.0 | 4.6
 | Euthanasia (unrelated to treatment or underlying disease | 1.1 | 0.0
 | Euthanasia (related to treatment or underlying disease | 0.0 | 2.3
 | Underlying Disease | 0.8 | 2.3
 | Undetermined | 1.1 | 6.8

In one small (n=15), uncontrolled field study in severely ill (Class 3) dogs, 5 dogs died following treatment. Pulmonary thromboembolism was the cause of one death. The remaining dogs were not necropsied. All 5 dogs were in right heart failure at the time of treatment. Clinical signs seen in this study which were not seen in the larger studies include atrial fibrillation, collapse, hypothermia, and weakness.

Post Approval Experience

In addition to the aforementioned adverse reactions reported in pre-approval clinical studies, there have also been rare reports of paresis and paralysis in dogs following administration of melarsomine dihydrochloride. To report suspected adverse drug events, for technical assistance or to obtain a copy of the SDS, contact Zoetis Inc. at 1-888-963-8471. For additional information about adverse drug experience reporting for animal drugs, contact FDA at 1-888-FDA-VETS or online at www.fda.gov/reportanimalae.

Overdosage

Three dogs were inadvertently overdosed with melarsomine dihydrochloride in the clinical field trials when the dose was calculated on a
mg/lb basis rather than a mg/kg basis (2X overdosage). Within 30 minutes of injection, one dog showed excessive
salivation, panting, restlessness, and fever with all signs resolving within 4 hours. Vomiting and
diarrhea were seen in the second dog within 24 hours of injection. The dog vomited once and the diarrhea resolved within 24 hours. The third dog showed no systemic reaction to the overdosage. Clinical observations in healthy beagle dogs after receiving up to 3X
the recommended dose included tremors, lethargy, unsteadiness/ataxia, restlessness, panting, shallow and labored respiration, rales, severe salivation, and vomiting which progressed to respiratory distress, collapse, cyanosis, stupor, and death (see SAFETY).

BAL in Oil Ampules (Dimercaprol Injection, USP) [Akorn, San Clemente, California, at 1-800-223-9851] is reported in the literature to be an antidote for arsenic toxicity and was shown in one study to reduce the signs of toxicity associated with overdosage of melarsomine dihydrochloride. The efficacy of melarsomine dihydrochloride may be reduced with co-administration of BAL.

EFFICACY

Results of the laboratory and clinical field trials demonstrate that treatment with melarsomine dihydrochloride results in reduction and/or clearance of D. immitis infection in dogs with Class 1, 2, and 3 heartworm disease. Evaluations for efficacy were
determined by post-mortem worm counts in the laboratory studies and detection of antigen in the
blood and subjective clinical assessments in the clinical trials. Physical exams, assessments of
clinical variables, class of heartworm disease, radiographic examinations, as well as complete
blood counts, serum chemistry profiles, and urinalysis were evaluated in the field trials.

Laboratory Studies

Placebo-controlled laboratory studies, melarsomine dihydrochloride, administered at
2.5 mg/kg twice, 24 hours apart, was 90.7% effective against transplanted adult heartworms and
90.8% effective against induced infections of 4 month old (L5) immature heartworms. To evaluate the
effectiveness of the alternate dosing regimen, dogs with transplanted heartworms were treated with
either 2.5 mg/kg once or 2.5 mg/kg once followed 1 month later with 2.5 mg/kg administered twice 24 hours apart. A single
injection of melarsomine dihydrochloride at 2.5 mg/kg reduced male worms 87.7% and female worms
16.9% (total 51.7%). When the full regime was used 100% of male worms and 98% of female worms were
killed (total 99%). Dogs with natural D. immitis infections were treated with melarsomine
dihydrochloride at 2.5 mg/kg twice, 24 hours apart. This dose was repeated 4 months later. Antigen
tests performed at month 4 showed a 90% conversion from antigen positive to negative status. Worm
counts at month 9 showed a 98.7% reduction in worm numbers as compared to placebo controls.

Clinical Field Studies

In two well-controlled field studies, 169 client-owned dogs, 1 to 12 years old and weighing 3.0 to 59.0 kg, with Class 1 or
stabilized Class 2 heartworm disease were treated with the recommended dose of melarsomine
dihydrochloride. In-office blood antigen tests were used pretreatment to diagnose the D. immitis infection and 4
months after drug administration to assess treatment response. At month 4, 76.2 to 81% of the dogs
had converted from antigen positive to antigen negative status. The conver- sion rate ranged from
89.7 to 98.2% after two treatment series. In an open-label study in 102 dogs, 1 to 18 years old and
weighing 4.4 to 40.8 kg, with Class 1 or stabilized Class 2 heartworm disease, the conversion
rate was 84% 4 months after one series of treatments. When a second series was given at month 4,
the conversion rate was 94%.

An open-label clinical field study was conducted in 44 dogs, 1.5 to 14 years old and weighing 3.2 to 50.0 kg, with stabilized, Class 3 heartworm disease. Dogs received the alternate dosing regime (2.5 mg/kg once followed 1 month later by 2.5
mg/kg twice 24 hours apart). The conversion rate was 89.2% 4 months after the final treatment. In a small, uncontrolled field trial (n=10) in Class 3 dogs the conversion rate was 100% 4 months after treatment.

DOSAGE AND ADMINISTRATION

DIROBAN should be administered ONLY by deep intramuscular injection in the epaxial (lumbar) muscles in the third and fifth lumbar region (see graphic). DO NOT ADMINISTER AT ANY OTHER SITE. Avoid superficial injection or leakage. Use a 23 gauge 1 inch needle for dogs equal to or less than 10 kg (22 lb) in weight. Use a 22 gauge 1½ inch needle for dogs greater than 10 kg (22 lb). Use alternating sides with each administration. If repeated administrations are warranted avoid injecting at the same lumbar location. Record the location of the first injection(s) in the patient’s medical record for future reference.

Disease Classification

It is vital to classify the severity of heartworm disease to apply the appropriate dosage regime for DIROBAN (see INDICATIONS).

Class 1 and 2

If necessary, dogs should be stabilized prior to treatment. DIROBAN should be administered
intramuscularly in the lumbar (L3 - L5) muscles at a dose of 2.5 mg/kg twice, 24 hours apart (see
Dosing Table). Four months follow- ing treatment, a second treatment series (2.5 mg/kg twice, 24
hours apart) can be elected taking into consid- eration the response to the first DIROBAN treatment
and the condition, age, and use of the dog. Worms that were too young to be killed by the first treatment series, i.e., < 4 months, may be killed by a second treatment series.

Class 3

Alternate Dosing Regime

Dogs with severe (Class 3) heartworm disease should be stabilized prior to treatment and then dosed intramuscularly in the
lumbar (L3 - L5) muscles with a single injection of 2.5 mg/kg then approximately 1 month later with 2.5 mg/kg administered twice 24 hours apart (see Dosing Table).

Dosing Table

Care must be taken to administer the proper dose. Accurately weigh the dog and calculate the volume to be injected based on the dose of 2.5 mg/kg (1.1 mg/lb). This is equivalent to 0.1 mL/kg (0.045 mL/lb). The following table should be used as a guide to ensure that the proper volume has been calculated.

WEIGHT (LB) | 2.2 | 4.4 | 6.6 | 8.8 | 11.0 | 13.2 | 15.4 | 17.6 | 19.8 | 22.0 | 44.0 | 66.0 | 88.0 | 110.0
WEIGHT (KG) | 1 | 2 | 3 | 4 | 5 | 6 | 7 | 8 | 9 | 10 | 20 | 30 | 40 | 50
VOLUME PER INJECTION | 0.1 | 0.2 | 0.3 | 0.4 | 0.5 | 0.6 | 0.7 | 0.8 | 0.9 | 1.0 | 2.0 | 3.0 | 4.0 | 5.0*

*Limited data were collected on the administration >5.0 mL at a single injection site

Preparation

DIROBAN should be aseptically reconstituted only with 2.0 mL of sterile water for injection (provided as 2.0 mL sterile water for
injection USP). This provides 2.5 mg melarsomine dihydrochloride per 0.1 mL of injectable solution. Two 50 mg vials will be required for dogs weighing > 20 kg and 40 kg and 3 vials will be required for dogs > 40 kg and 60 kg. Use immediately. Reconstituted solution may be used within 36 hours if refrigerated and kept from light.

Treatment Response

A baseline can be established pre-treatment by using commercially available in-office heartworm antigen test kits prior to
treatment. Treatment response can be assessed best by heartworm antigen testing applied 4 months after
treatment. A successful treatment is determined to be conversion from an antigen positive to an
antigen negative status. In dogs with signs of heartworm disease, gradual improvement should be
observed as the long-term effects of the heartworm infection resolve. Some dogs may have chronic effects that will not totally resolve.

CONCOMITANT THERAPY

During the course of clinical field trials, DIROBAN was administered concurrently with anti-inflammatories, antibiotics, insecticides, heartworm prophylactics, and various other drugs commonly used to stabilize and support dogs with heartworm disease with no adverse drug interactions noted.

Routine Prophylaxis

If the dog is not currently receiving commercially available heartworm preventatives, they may be administered consistent with label recommendations and re-exposure risk.

STORAGE CONDITIONS

Store upright at controlled room temperature (20°- 25°C). After reconstitution, solutions should be stored under refrigeration and kept from light in the original packaging for 36 hours. Do not freeze reconstituted solution.
No antimicrobial or other substance has been added to the sterile water diluent.

HOW SUPPLIED

DIROBAN is provided as: 5 - 50 mg vials of lyophilized melarsomine dihydrochloride with accompanying 5 - 2 mL vials of sterile water for injection.

Approved by FDA under ANADA # 200-609
zoetis
Distributed by:
Zoetis Inc.
Kalamazoo, MI 49007
Revised: January 2020

40028760